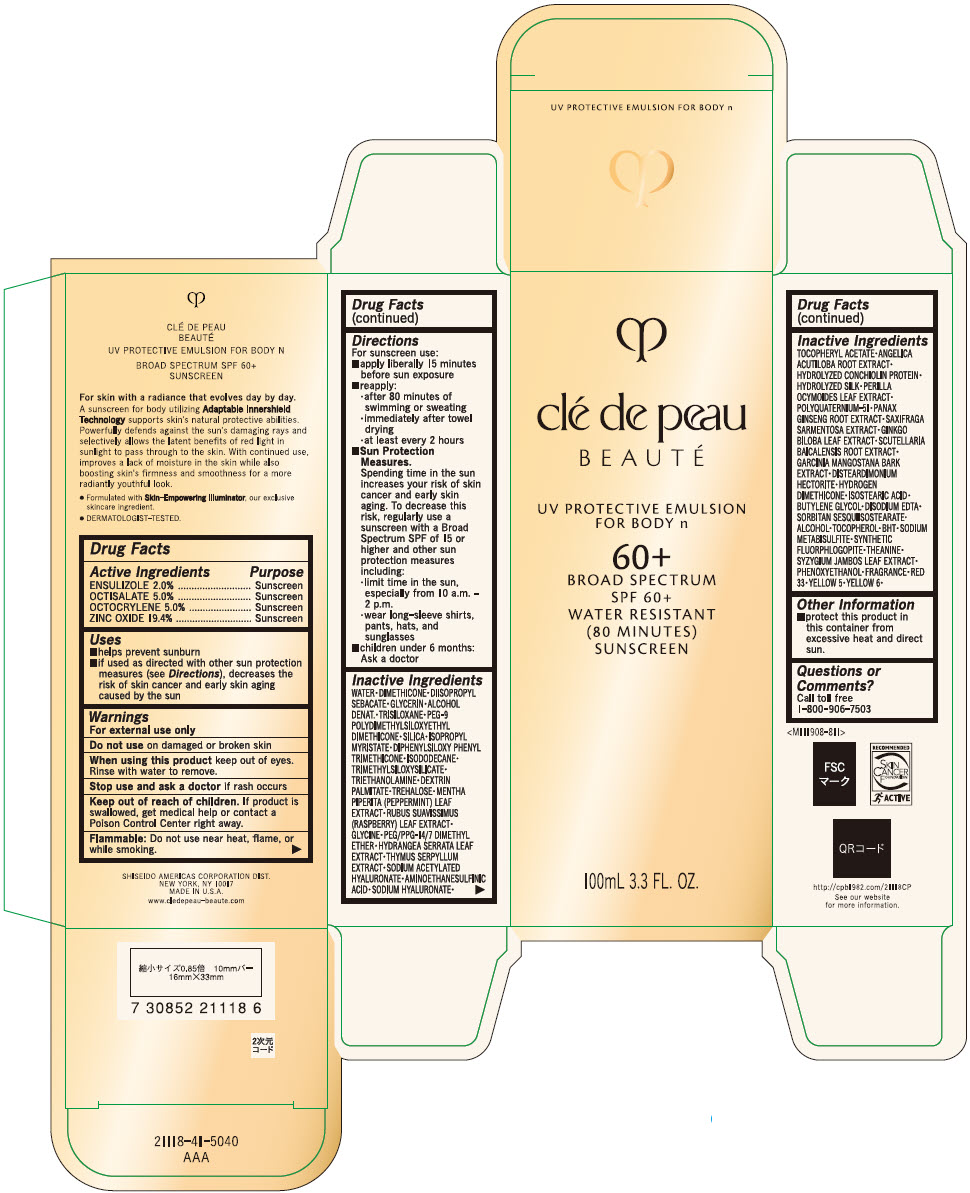 DRUG LABEL: cle de peau BEAUTE UV PROTECTIVE FOR BODY n
NDC: 58411-858 | Form: EMULSION
Manufacturer: SHISEIDO AMERICAS CORPORATION
Category: otc | Type: HUMAN OTC DRUG LABEL
Date: 20230530

ACTIVE INGREDIENTS: ENSULIZOLE 2.384 g/100 mL; OCTISALATE 5.96 g/100 mL; OCTOCRYLENE 5.96 g/100 mL; ZINC OXIDE 23.1248 g/100 mL
INACTIVE INGREDIENTS: WATER; DISTEARDIMONIUM HECTORITE; FD&C YELLOW NO. 5; FD&C YELLOW NO. 6; HYPOTAURINE; GLYCERIN; GLYCINE; HYDRANGEA SERRATA LEAF; POLYQUATERNIUM-51 (2-METHACRYLOYLOXYETHYL PHOSPHORYLCHOLINE/N-BUTYL METHACRYLATE; 3:7); SODIUM ACETYLATED HYALURONATE; THEANINE; PEG-9 POLYDIMETHYLSILOXYETHYL DIMETHICONE; ISOPROPYL MYRISTATE; ISOSTEARIC ACID; PEG/PPG-14/7 DIMETHYL ETHER; SYZYGIUM JAMBOS LEAF; DIPHENYLSILOXY PHENYL TRIMETHICONE; GARCINIA MANGOSTANA BARK; HYDROGEN DIMETHICONE (13 CST); PHENOXYETHANOL; SILICON DIOXIDE; SODIUM METABISULFITE; BUTYLATED HYDROXYTOLUENE; SORBITAN SESQUIISOSTEARATE; .ALPHA.-TOCOPHEROL; .ALPHA.-TOCOPHEROL ACETATE, DL-; TROLAMINE; TRIMETHYLSILOXYSILICATE (M/Q 0.6-0.8); BUTYLENE GLYCOL; HYALURONATE SODIUM; ISODODECANE; DEXTRIN PALMITATE (CORN; 20000 MW); TRISILOXANE; ALCOHOL; D&C RED NO. 33; TREHALOSE; DIISOPROPYL SEBACATE; DIMETHICONE; ANGELICA ACUTILOBA ROOT; GINKGO; MENTHA PIPERITA LEAF; ASIAN GINSENG; PERILLA FRUTESCENS LEAF; EDETATE DISODIUM; SAXIFRAGA STOLONIFERA LEAF; THYMUS SERPYLLUM WHOLE; RUBUS CHINGII VAR. SUAVISSIMUS LEAF; SCUTELLARIA BAICALENSIS ROOT

clé de peau BEAUTÉ UV PROTECTIVE EMULSION FOR BODY n

Drug Facts

ACTIVE INGREDIENT

Active ingredients | Purpose
ENSULIZOLE 2.0% | Sunscreen
OCTISALATE 5.0% | Sunscreen
OCTOCRYLENE 5.0% | Sunscreen
ZINC OXIDE 19.4% | Sunscreen

Uses

- helps prevent sunburn
- if used as directed with other sun protection measures (see Directions), decreases the risk of skin cancer and early skin aging caused by the sun

Warnings

For external use only

Do not use on damaged or broken skin

When using this product keep out of eyes. Rinse with water to remove.

Stop use and ask a doctor if rash occurs

Keep out of reach of children. If product is swallowed, get medical help or contact a Poison Control Center right away.

Flammable: Do not use near heat, flame, or while smoking.

Directions

For sunscreen use:

- apply liberally 15 minutes before sun exposure
- reapply:
  - after 80 minutes of swimming or sweating
  - immediately after towel drying
  - at least every 2 hours
- Sun Protection Measures. Spending time in the sun increases your risk of skin cancer and early skin aging. To decrease this risk, regularly use a sunscreen with a Broad Spectrum SPF of 15 or higher and other sun protection measures including:
  - limit time in the sun, especially from 10 a.m. – 2 p.m.
  - wear long-sleeve shirts, pants, hats, and sunglasses
- children under 6 months: Ask a doctor

Inactive Ingredients

WATER∙ DIMETHICONE∙ DIISOPROPYL SEBACATE ∙GLYCERIN∙ ALCOHOL DENAT. • TRISILOXANE∙ PEG-9 POLYDIMETHYLSILOXYETHYL DIMETHICONE ∙SILICA∙ ISOPROPYL MYRISTATE∙ DIPHENYLSILOXY PHENYL TRIMETHICONE • ISODODECANE • TRIMETHYLSILOXYSILICATE • TRIETHANOLAM IN E • DEXTRIN PALMITATE • TREHALOSE • MENTHA PIPERITA (PEPPERMINT) LEAF EXTRACT∙ RUBUS SUAVISSIMUS (RASPBERRY) LEAF EXTRACT∙ GLYCINE∙ PEG/PPG-14/7 DIMETHYL ETHER∙ HYDRANGEA SERRATA LEAF EXTRACT∙ THYMUS SERPYLLUM EXTRACT∙ SODIUM ACETYLATED HYALURONATE ∙AMINOETHANESULFINIC ACID∙SODIUM HYALURONATE∙ TOCOPHERYL ACETATE-ANGELICA ACUTILOBA ROOT EXTRACT∙ HYDROLYZED CONCHIOLIN PROTEIN∙ HYDROLYZED SILK∙ PERILLA OCYMOIDES LEAF EXTRACT∙ POLYQUATERNIUM-51 • PANAX GINSENG ROOT EXTRACT∙SAXIFRAGA SARMENTOSA EXTRACT∙ GINKGO BILOBA LEAF EXTRACT-SCUTELLARIA BAICALENSIS ROOT EXTRACT∙ GARCINIA MANGOSTANA BARK EXTRACT∙ DISTEARDIMONIUM HECTORITE∙ HYDROGEN DIMETHICONE∙ ISOSTEARIC ACID∙ BUTYLENE GLYCOL∙DISODIUM EDTA∙ SORBITAN SESQUIISOSTEARATE∙ ALCOHOL∙ TOCOPHEROL∙ BHT • SODIUM M ETABISULFITE • SYNTHETIC FLUORPHLOGOPITE • THEANINE • SYZYGIUM JAMBOS LEAF EXTRACT∙ PHENOXYETHANOL ∙FRAGRANCE∙ RED 33∙YELLOW 5∙YELLOW 6∙

Other Information

- protect this product in this container from excessive heat and direct sun.

Questions or Comments?

Call toll free 1-800-906-7503

PRINCIPAL DISPLAY PANEL - 100 mL Container Carton

clé de peau
BEAUTÉ

UV PROTECTIVE EMULSION
FOR BODY n

60+
BROAD SPECTRUM
SPF 60+
WATER RESISTANT
(80 MINUTES)
SUNSCREEN

100mL 3.3 FL. OZ.